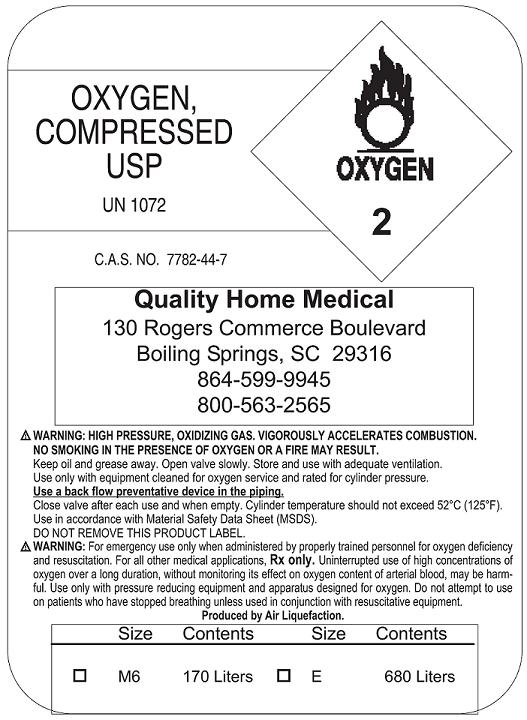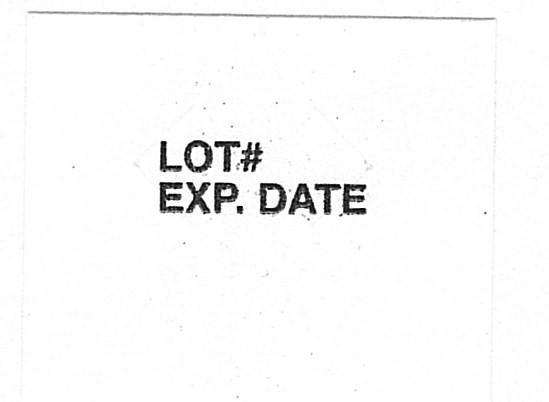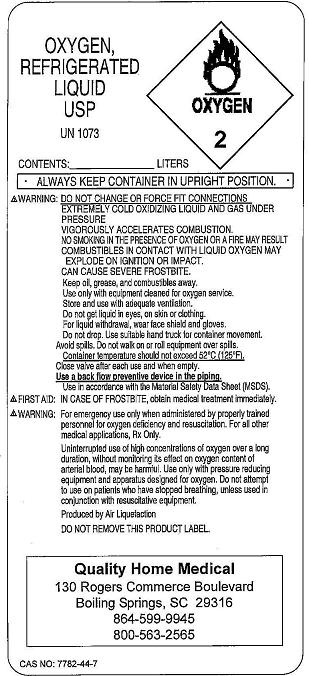 DRUG LABEL: Oxygen
NDC: 10163-0202 | Form: GAS
Manufacturer: Quality Home Medical, Inc. 
Category: prescription | Type: HUMAN PRESCRIPTION DRUG LABEL
Date: 20121102

ACTIVE INGREDIENTS: Oxygen 99 L/100 L

Oxygen

Principal for Oxygen Product

High Pressure Oxygen Label

Lot Sticker

Liquid Label